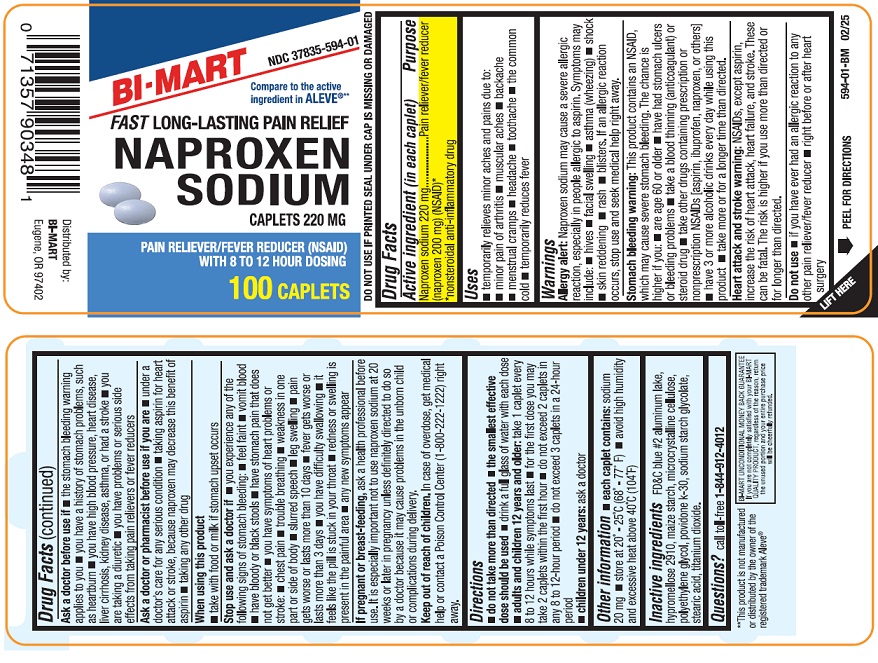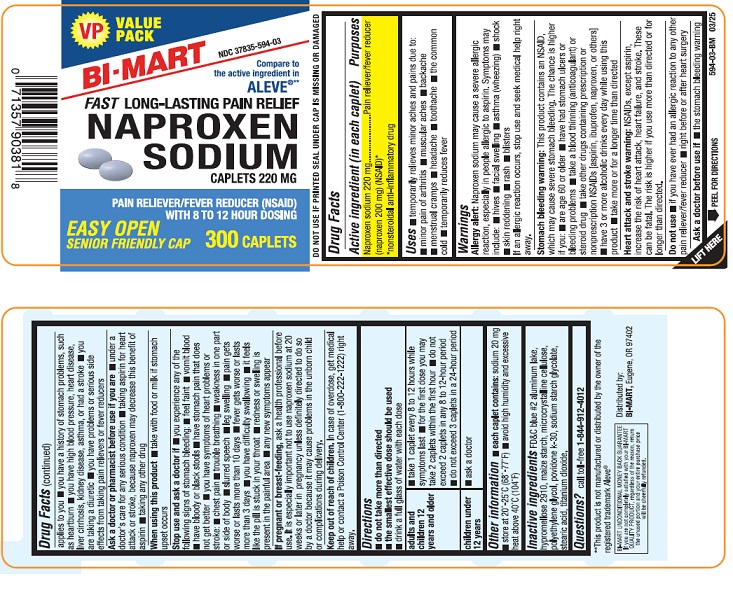 DRUG LABEL: Naproxen Sodium
NDC: 37835-594 | Form: TABLET
Manufacturer: Bi-Mart
Category: otc | Type: HUMAN OTC DRUG LABEL
Date: 20250301

ACTIVE INGREDIENTS: NAPROXEN SODIUM 220 mg/1 1
INACTIVE INGREDIENTS: FD&C BLUE NO. 2 ALUMINUM LAKE; HYPROMELLOSES; STARCH, CORN; CELLULOSE, MICROCRYSTALLINE; POLYETHYLENE GLYCOL, UNSPECIFIED; POVIDONE K30; SODIUM STARCH GLYCOLATE TYPE A POTATO; STEARIC ACID; TITANIUM DIOXIDE

ACTIVE INGREDIENT

(in each caplet)
Naproxen sodium 220 mg (Naproxen 200 mg) (NSAID)*
*nonsteroidal anti-inflammatory drug

PURPOSE

Pain reliever/fever reducer

USES

• temporarily relieves minor aches and pains due to:
• minor pain of arthritis
• muscular aches
• backache
• menstrual cramps
• headache
• toothache
• the common cold
• temporarily reduces fever

WARNINGS

Allergy alert:

Naproxen sodium may cause a severe allergic reaction, especially in people allergic to aspirin. Symptoms may include:

• hives
• facial swelling
• asthma (wheezing)
• shock
• skin reddening
• rash
• blisters
If an allergic reaction occurs, stop use and seek medical help right away.
Stomach bleeding warning:

This product contains an NSAID, which may cause severe stomach bleeding. The chance is higher if you:

• are age 60 or older
• have had stomach ulcers or bleeding problems
• take a blood thinning (anticoagulant) or steroid drug
• take other drugs containing prescription or nonprescription NSAIDs [aspirin, ibuprofen, naproxen, or others]
• have 3 or more alcoholic drinks every day while using this product
• take more or for a longer time than directed

Heart attack and stroke warning:
NSAIDs, except aspirin, increase the risk of heart attack, heart failure, and stroke. These can be fatal. The risk is higher if you use more than directed or for longer than directed.

DO NOT USE

• if you have ever had an allergic reaction to any other pain reliever/fever reducer
• right before or after heart surgery

ASK A DOCTOR BEFORE USE IF

• the stomach bleeding warning applies to you
• you have a history of stomach problems, such as heartburn
• you have had high blood pressure, heart disease, liver cirrhosis, kidney disease, asthma, or had a stroke
• you are taking a diuretic
• you have problems or serious side effects from taking pain relievers or fever reducers

ASK A DOCTOR OR PHARMACIST BEFORE USE IF YOU ARE

• under a doctor's care for any serious condition

• taking aspirin for heart attack or stroke, because naproxen may decrease this benifits of aspirin

• taking any other drug

WHEN USING THIS PRODUCT

• take with food or milk if stomach upset occurs

STOP USE AND ASK DOCTOR IF

• you experience any of the following signs of stomach bleeding:
•feel faint
•vomit blood
•have bloody or black stools
•have stomach pain that does not get better
• you have symptoms of heart problems or stroke:
•chest pain
•trouble breathing
•weakness in one part or side of body
•slurred speech
•leg swelling
• pain gets worse or lasts more than 10 days
• fever gets worse or lasts more than 3 days
• you have difficulty swallowing
• it feels like the pill is stuck in your throat
• redness or swelling is present in the painful area
• any new symptoms appear

PREGNANCY/BREASTFEEDING

If pregnant or breast-feeding,ask a health professional before use. It is especially important not to use naproxen sodium at 20 weeks or later in pregnancy unless definitely directed to do so by a doctor because it may cause problems in the unborn child or complications during delivery.

KEEP OUT OF REACH OF CHILDREN

In case of overdose, get medical help or contact a Poison Control Center (1-800-222-1222) right away.

DIRECTIONS

• do not take more than directed
• the smallest effective dose should be used
• drink a full glass of water with each dose

adults and children 12 years and older | - take 1 caplet every 8 to 12 hours while symptoms last - for the first dose you may take 2 caplets within the first hour - do not exceed 2 caplets in any 8 to 12 hour period - do not exceed 3 caplets in a 24 hour period
children under 12 years | - ask a doctor

OTHER INFORMATION

- each caplet contains:sodium 20 mg
- store at 20 - 25°C (68 - 77°F).
- avoid high humidity and excessive heat above 40°C (104°F)
- DO NOT USE IF PRINTED SEAL UNDER CAP IS MISSING OR DAMAGED

INACTIVE INGREDIENTS

FD&C blue#2 aluminum lake, hypromellose 2910, maize starch, microcrystalline cellulose, polyethylene glycol, povidone k-30, sodium starch glycolate, stearic acid, titanium dioxide

QUESTIONS?

call toll free 1-844-912-4012

Distributed by:

BI-MART

Eugene, OR 97402

PRINCIPAL DISPLAY PANEL-100 Count

NDC 37835-594-01

Compare to the active ingredients in ALEVE®**

FAST LONG-LASTING PAIN RELIEF

NAPROXEN SODIUM

CAPLETS 220 MG

PAIN RELIEVER/FEVER REDUCER (NSAID)

WITH 8 TO 12 HOUR DOSING

100 Caplets

**This product is not manufactured or distributed by the owner of the registered trademark ALEVE®.

PRINCIPAL DISPLAY PANEL-300 Count

NDC 37835-594-03

Compare to the active ingredients in ALEVE®**

FAST LONG-LASTING PAIN RELIEF

NAPROXEN SODIUM

CAPLETS 220 MG

PAIN RELIEVER/FEVER REDUCER (NSAID)

WITH 8 TO 12 HOUR DOSING

300 Caplets

**This product is not manufactured or distributed by the owner of the registered trademark ALEVE®.